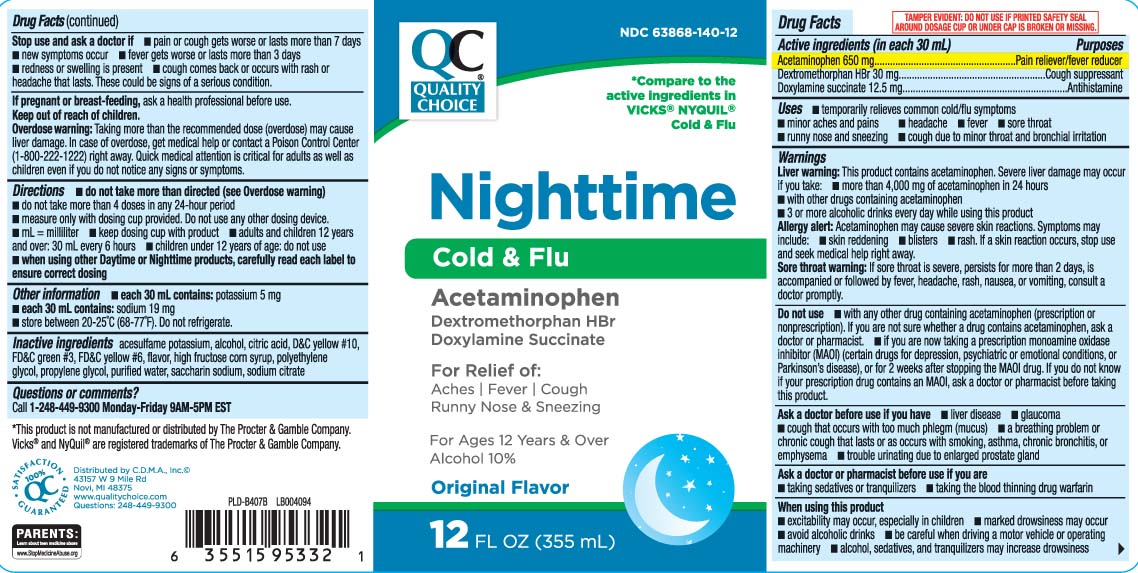 DRUG LABEL: Cold and Flu
NDC: 63868-140 | Form: LIQUID
Manufacturer: QUALITY CHOICE (Chain Drug Marketing Association)
Category: otc | Type: HUMAN OTC DRUG LABEL
Date: 20251216

ACTIVE INGREDIENTS: ACETAMINOPHEN 650 mg/30 mL; DEXTROMETHORPHAN HYDROBROMIDE 30 mg/30 mL; DOXYLAMINE SUCCINATE 12.5 mg/30 mL
INACTIVE INGREDIENTS: PROPYLENE GLYCOL; WATER; ACESULFAME POTASSIUM; ALCOHOL; ANHYDROUS CITRIC ACID; HIGH FRUCTOSE CORN SYRUP; POLYETHYLENE GLYCOL, UNSPECIFIED; SACCHARIN SODIUM; TRISODIUM CITRATE DIHYDRATE; D&C YELLOW NO. 10; FD&C GREEN NO. 3; FD&C YELLOW NO. 6

Drug Facts

Active ingredients (in each 30 mL)

Acetaminophen 650 mg

Dextromethorphan HBr 30 mg

Doxylamine succinate 12.5 mg

Purposes

Pain reliever/fever reducer

Cough suppressant

Antihistamine

Uses

- temporarily relieves these common cold/flu symptoms:
  - minor aches and pains
  - headache
  - sore throat
  - fever
  - runny nose and sneezing
  - cough due to minor throat and bronchial irritation

Warnings

Liver warning: This product contains acetaminophen. Severe liver damage may occur if you take

- more than 4,000 doses of acetaminophen in 24 hours
- with other drugs containing acetaminophen
- 3 or more alcoholic drinks every day while using this product

Allergy alert: Acetaminophen may cause severe skin reactions. Symptoms may include:

- skin reddening
- blisters
- rash

If a skin reaction occurs, stop use and seek medical help right away.

Sore throat warning: If sore throat is severe, persists for more than 2 days, is accompanied or followed by fever, headache, rash, nausea, or vomiting, consult a doctor promptly.

Do not use

- if you are now taking a prescription monoamine oxidase inhibitor (MAOI) (certain drugs for depression, psychiatric or emotional conditions, or Parkinson’s disease), or for 2 weeks after stopping the MAOI drug. If you do not know if your prescription drug contains an MAOI, ask a doctor or pharmacist before taking this product.
- with any other drug containing acetaminophen (prescription or non-prescription). If you are not sure whether a drug contains acetaminophen, ask a doctor or pharmacist

Ask a doctor before use if you have

- liver disease
- glaucoma
- cough that occurs with too much phlegm (mucus)
- a breathing problem or chronic cough that that lasts or occurs with smoking, asthma, chronic bronchitis, or emphysema
- trouble urinating due to an enlarged prostate gland

Ask a doctor or pharmacist before use if you are taking

- sedatives or tranquilizers
- the blood thinning drug warfarin

When using this product

- excitability may occur, especially in children
- marked drowsiness may occur
- avoid alcoholic drinks
- be careful when driving a motor vehicle or operating machinery
- alcohol, sedatives and tranquilizers may increase drowsiness

Stop use and ask a doctor if

- pain or cough gets worse or lasts more than 7 days
- new symptoms occur
- fever gets worse or lasts more than 7 days
- redness or swelling is present
- cough comes back or occurs with rash or headache that lasts.

These could be signs of a serious condition.

If pregnant or breast-feeding,

ask a health professional before use.

Keep out of reach of children.

Overdose warning: Taking more than the recommended dose (overdose) may cause liver damage. In case of overdose, get medical help or contact a Poison Control Center (1-800-222-1222) right away. Quick medical attention is critical for adults as well as for children even if you do not notice any signs or symptoms.

Directions

- do not take more than directed (see Overdose warning)
- do not take more than 4 doses in any 24-hours period
- measure only with dosing cup provided. Do not use any other dosing device.
- mL= milliliter
- keep dosing cup with product
- adults and children 12 years and over: 30 mL every 6 hours
- children under 12 years of age: do not use
- When using other Day Time or Night Time products, carefully read each label to ensure correct dosing

Other information

- each 30 mL contains: potassium 5 mg
- each 30 mL contains: Sodium 19 mg
- store between 20-25ºC (68-77ºF). Do not refrigerate.

Inactive ingredients

acesulfame potassium, alcohol, citric acid, D&C yellow #10, FD&C green #3, FD&C yellow #6,, flavor,high fructose corn syrup, polyethylene glycol, propylene glycol, purified water, saccharin sodium, sodium citrate

Questions or comments?

Call 1-248-449-9300 Monday-Friday 9AM-5PM EST

Principal Display Panel

*Compare to the active ingredients in VICKS® NYQUIL® Cold & Flu

Nighttime Cold & Flu

Acetaminophen

Dextromethorphan

Doxylamine succinate

For Relief of:

Aches | Fever | Cough

Runny Nose & Sneezing

For Ages 12 Years & Over

Alcohol 10 %

Original Flavor

FL OZ (mL)

*This product is not manufactured or distributed by The Procter & Gamble Company. Vicks® and NyQuil® are registered trademarks of The Procter & Gamble Company.

TAMPER EVIDENT: DO NOT USE IF PRINTED SAFETY SEAL AROUND DOSAGE CUP OR UNDER CAP IS BROKEN OR MISSING.

Distributed by C.D.M.A., Inc.©

43157 W. 9 Mile Rd

Novi, MI 48376-0995

www.qualitychoice.com

Product Label

QUALITY CHOICE Nighttime Cold & Flu